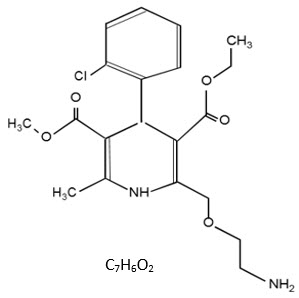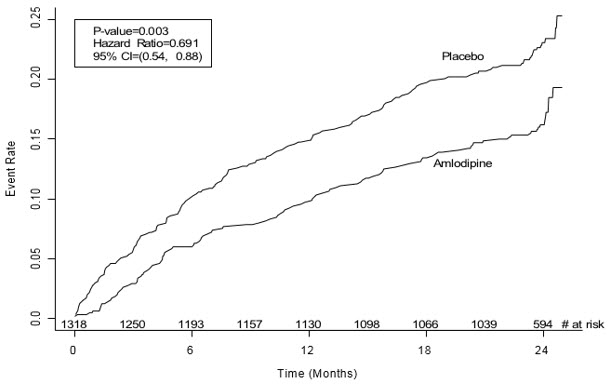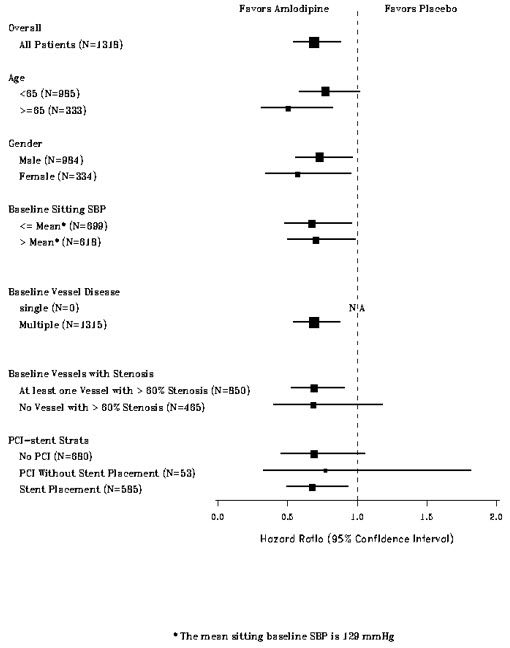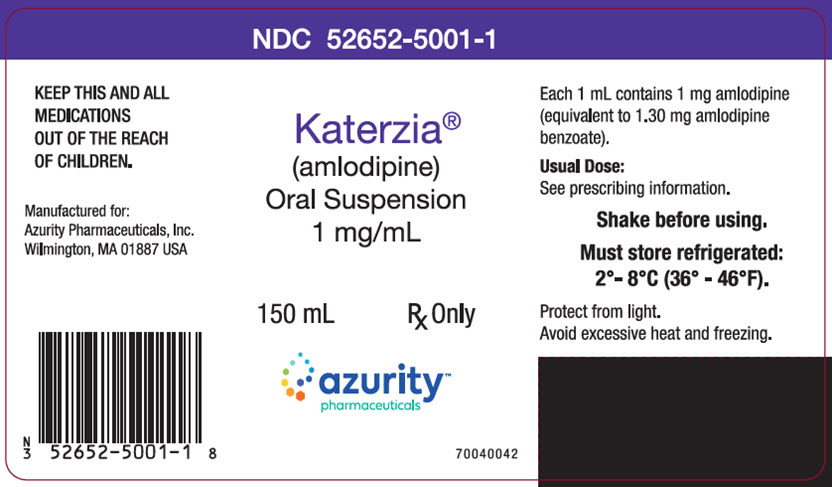 DRUG LABEL: Katerzia
NDC: 52652-5001 | Form: SUSPENSION
Manufacturer: Azurity Pharmaceuticals, Inc.
Category: prescription | Type: HUMAN PRESCRIPTION DRUG LABEL
Date: 20251216

ACTIVE INGREDIENTS: AMLODIPINE BENZOATE 1 mg/1 mL
INACTIVE INGREDIENTS: CITRIC ACID MONOHYDRATE; SILICON DIOXIDE; HYPROMELLOSE, UNSPECIFIED; MALTODEXTRIN; POLYSORBATE 80; SODIUM BENZOATE; SODIUM CITRATE, UNSPECIFIED FORM; SUCRALOSE; WATER

HIGHLIGHTS OF PRESCRIBING INFORMATION

These highlights do not include all the information needed to use KATERZIA®safely and effectively. See full prescribing information for KATERZIA®.
KATERZIA (amlodipine) oral suspension, for oral use.
Initial U.S. Approval: 1992

1 INDICATIONS AND USAGE

KATERZIA is a calcium channel blocker and may be used alone or in combination with other antihypertensive and antianginal agents for the treatment of:

- Hypertension (1.1)
  - KATERZIA is indicated for the treatment of hypertension in adults and children 6 years and older, to lower blood pressure. Lowering blood pressure reduces the risk of fatal and nonfatal cardiovascular events, primarily strokes and myocardial infarctions.
- Coronary Artery Disease (1.2)
  - Chronic Stable Angina
  - Vasospastic Angina (Prinzmetal’s or Variant Angina)
  - Angiographically Documented Coronary Artery Disease in patients without heart failure or an ejection fraction < 40%.

2 DOSAGE AND ADMINISTRATION

- Adult recommended starting dose: 5 mg orally once daily with maximum dose 10 mg once daily. (2.1)
  - Small, fragile, or elderly patients, or patients with hepatic insufficiency may be started on 2.5 mg once daily. (2.1)
- Pediatric starting dose: 2.5 mg to 5 mg once daily. (2.2)

Important Limitation: Doses in excess of 5 mg daily have not been studied in pediatric patients. (2.2)
SHAKE BEFORE USING

3 DOSAGE FORMS AND STRENGTHS

- Oral suspension: 1 mg/mL. (3)

4 CONTRAINDICATIONS

- Known sensitivity to amlodipine. (4)

5 WARNINGS AND PRECAUTIONS

- Symptomatic hypotension is possible, particularly in patients with severe aortic stenosis. However, acute hypotension is unlikely. (5.1)
- Worsening angina and acute myocardial infarction can develop after starting or increasing the dose of amlodipine, particularly in patients with severe obstructive coronary artery disease. (5.2)
- Titrate slowly in patients with severe hepatic impairment. (5.3)

6 ADVERSE REACTIONS

Most common adverse reaction to amlodipine is edema which occurred in a dose related manner. Other adverse experiences not dose related but reported with an incidence >1.0% are fatigue, nausea, abdominal pain, and somnolence. (6)

To report SUSPECTED ADVERSE REACTIONS, contact Azurity Pharmaceuticals, Inc., at 1-800-461-7449 or FDA at 1-800-FDA-1088 or www.fda.gov/medwatch.

7 DRUG INTERACTIONS

- Do not exceed doses greater than 20 mg daily of simvastatin. (7.2)

8 USE IN SPECIFIC POPULATIONS

- Pediatric: Effect on patients less than 6 years old is not known. (8.4)
- Geriatric: Start dosing at the low end of the dose range. (8.5)

FULL PRESCRIBING INFORMATION

1 INDICATIONS AND USAGE

1.1 Hypertension

KATERZIA is indicated for the treatment of hypertension in adults and children 6 years and older, to lower blood pressure. Lowering blood pressure reduces the risk of fatal and nonfatal cardiovascular events, primarily strokes and myocardial infarctions. These benefits have been seen in controlled trials of antihypertensive drugs from a wide variety of pharmacologic classes including amlodipine.

Control of high blood pressure should be part of comprehensive cardiovascular risk management, including, as appropriate, lipid control, diabetes management, antithrombotic therapy, smoking cessation, exercise, and limited sodium intake. Many patients will require more than one drug to achieve blood pressure goals. For specific advice on goals and management, see published guidelines, such as those of the National High Blood Pressure Education Program’s Joint National Committee on Prevention, Detection, Evaluation, and Treatment of High Blood Pressure (JNC).

Numerous antihypertensive drugs, from a variety of pharmacologic classes and with different mechanisms of action, have been shown in randomized controlled trials to reduce cardiovascular morbidity and mortality, and it can be concluded that it is blood pressure reduction, and not some other pharmacologic property of the drugs, that is largely responsible for those benefits. The largest and most consistent cardiovascular outcome benefit has been a reduction in the risk of stroke, but reductions in myocardial infarction and cardiovascular mortality also have been seen regularly.

Elevated systolic or diastolic pressure causes increased cardiovascular risk, and the absolute risk increase per mmHg is greater at higher blood pressures, so that even modest reductions of severe hypertension can provide substantial benefit. Relative risk reduction from blood pressure reduction is similar across populations with varying absolute risk, so the absolute benefit is greater in patients who are at higher risk independent of their hypertension (for example, patients with diabetes or hyperlipidemia), and such patients would be expected to benefit from more aggressive treatment to a lower blood pressure goal.

Some antihypertensive drugs have smaller blood pressure effects (as monotherapy) in black patients, and many antihypertensive drugs have additional approved indications and effects (e.g., on angina, heart failure, or diabetic kidney disease). These considerations may guide selection of therapy.

KATERZIA may be used alone or in combination with other antihypertensive agents.

1.2 Coronary Artery Disease (CAD)

Chronic Stable Angina
KATERZIA is indicated for the symptomatic treatment of chronic stable angina. KATERZIA may be used alone or in combination with other antianginal agents.

Vasospastic Angina (Prinzmetal’s or Variant Angina)
KATERZIA is indicated for the treatment of confirmed or suspected vasospastic angina. KATERZIA may be used as monotherapy or in combination with other antianginal agents.

Angiographically Documented CAD
In patients with recently documented CAD by angiography and without heart failure or an ejection fraction <40%, KATERZIA is indicated to reduce the risk of hospitalization for angina and to reduce the risk of a coronary revascularization procedure.

2 DOSAGE AND ADMINISTRATION

2.1 Adults

The usual initial antihypertensive oral dose of KATERZIA is 5 mg orally once daily, and the maximum dose is 10 mg once daily.

Small, fragile, or elderly patients, or patients with hepatic insufficiency may be started on 2.5 mg once daily and this dose may be used when adding KATERZIA to other antihypertensive therapy [see Use in Specific Populations (8.6)] .

Adjust dosage according to blood pressure goals. In general, wait 7 to 14 days between titration steps. Titrate more rapidly, however, if clinically warranted, provided the patient is assessed frequently.

Angina: The recommended dose for chronic stable or vasospastic angina is 5 to 10 mg once daily, with the lower dose suggested in the elderly and in patients with hepatic insufficiency. Most patients will require 10 mg once daily for adequate effect.

Coronary artery disease: The recommended dose range for patients with coronary artery disease is 5 to 10 mg once daily. In clinical studies, the majority of patients required 10 mg once daily [see Clinical Studies (14.4)] .

2.2 Children

The effective antihypertensive oral dose in pediatric patients ages 6 to 17 years is 2.5 to 5 mg once daily. Doses in excess of 5 mg daily have not been studied in pediatric patients [see Clinical Pharmacology (12.3), Clinical Studies (14.1)] .

3 DOSAGE FORMS AND STRENGTHS

KATERZIA oral suspension contains 1 mg/mL of amlodipine (equivalent to 1.30 mg of amlodipine benzoate) in an aqueous, white to off-white, liquid suspension.

4 CONTRAINDICATIONS

KATERZIA is contraindicated in patients with known sensitivity to amlodipine.

5 WARNINGS AND PRECAUTIONS

5.1 Hypotension

Symptomatic hypotension is possible, particularly in patients with severe aortic stenosis. Because of the gradual onset of action, acute hypotension is unlikely.

5.2 Increased Angina or Myocardial Infarction

Worsening angina and acute myocardial infarction can develop after starting or increasing the dose of KATERZIA, particularly in patients with severe obstructive coronary artery disease.

5.3 Patients with Hepatic Failure

Because KATERZIA is extensively metabolized by the liver and the plasma elimination half-life (t1/2) is 56 hours in patients with impaired hepatic function, titrate slowly when administering KATERZIA to patients with severe hepatic impairment.

6 ADVERSE REACTIONS

6.1 Clinical Trials Experience

Because clinical trials are conducted under widely varying conditions, adverse reaction rates observed in the clinical trials of a drug cannot be directly compared to rates in the clinical trials of another drug and may not reflect the rates observed in practice.

Amlodipine has been evaluated for safety in more than 11,000 patients in U.S. and foreign clinical trials. In general, treatment with amlodipine was well-tolerated at doses up to 10 mg daily. Most adverse reactions reported during therapy with amlodipine were of mild or moderate severity. In controlled clinical trials directly comparing amlodipine (N=1730) at doses up to 10 mg to placebo (N=1250), discontinuation of amlodipine because of adverse reactions was required in about 1.5% of patients and was not different from placebo (about 1%). The most commonly reported adverse reactions more frequent than placebo are reflected in the table below. The incidence (%) of adverse reactions that occurred in a dose related manner are as follows:

Table 1: Most Common Dose-Related Adverse Events Compared to Placebo
 |  | Amlodipine |  | Placebo
 | 2.5 mg | 5 mg | 10 mg | N=520
 | N=275 | N=296 | N=268 | N=520
Edema | 1.8 | 3.0 | 10.8 | 0.6
Dizziness | 1.1 | 3.4 | 3.4 | 1.5
Flushing | 0.7 | 1.4 | 2.6 | 0.0
Palpitation | 0.7 | 1.4 | 4.5 | 0.6

Other adverse reactions that were not clearly dose related but were reported with an incidence greater than 1.0% in placebo-controlled clinical trials included the following:

Table 2: Other Adverse Events with a Reported Incidence Greater Than 1%
 | Amlodipine (%) | Placebo (%)
 | (N=1730) | (N=1250)
Fatigue | 4.5 | 2.8
Nausea | 2.9 | 1.9
Abdominal Pain | 1.6 | 0.3
Somnolence | 1.4 | 0.6

For several adverse experiences that appear to be drug and dose related, there was a greater incidence in women than men associated with amlodipine treatment as shown in the following table:

Table 3: Comparison of Drug and Dose-Related Adverse Events Reported by Men and Women
 | Amlodipine |  | Placebo
 | Male=% | Female=% | Male=% | Female=%
 | (N=1218) | (N=512) | (N=914) | (N=336)
Edema | 5.6 | 14.6 | 1.4 | 5.1
Flushing | 1.5 | 4.5 | 0.3 | 0.9
Palpitations | 1.4 | 3.3 | 0.9 | 0.9

6.2 Postmarketing Experience

Because these reactions are reported voluntarily from a population of uncertain size, it is not always possible to reliably estimate their frequency or establish a causal relationship to drug exposure.

General: gynecomastia.

Hepatic: jaundice and hepatic enzyme elevations, some requiring hospitalization

Neurologic: extrapyramidal disorder

7 DRUG INTERACTIONS

7.1 Impact of Other Drugs on Amlodipine

CYP3A Inhibitors

Co-administration with CYP3A inhibitors (moderate and strong) results in increased systemic exposure to amlodipine and may require dose reduction. Monitor for symptoms of hypotension and edema when amlodipine is co-administered with CYP3A inhibitors to determine the need for dose adjustment [see Clinical Pharmacology (12.3)] .

CYP3A Inducers

No information is available on the quantitative effects of CYP3A inducers on amlodipine. Blood pressure should be closely monitored when amlodipine is co-administered with CYP3A inducers.

7.2 Impact of Amlodipine on Other Drugs

Simvastatin

Co-administration of simvastatin with amlodipine increases the systemic exposure of simvastatin. Limit the dose of simvastatin in patients on amlodipine to 20 mg daily [see Clinical Pharmacology (12.3)] .

Immunosuppressants

Amlodipine may increase the systemic exposure of cyclosporine or tacrolimus when co‑administered. Frequent monitoring of trough blood levels of cyclosporine and tacrolimus is recommended and adjust the dose when appropriate [see Clinical Pharmacology (12.3)] .

8 USE IN SPECIFIC POPULATIONS

8.1 Pregnancy

Risk Summary

The limited available data based on post-marketing reports with amlodipine use in pregnant women are not sufficient to inform a drug-associated risk for major birth defects and miscarriage. There are risks to the mother and fetus associated with poorly controlled hypertension in pregnancy (see Clinical Considerations) . In animal reproduction studies, there was no evidence of adverse developmental effects when pregnant rats and rabbits were treated orally with amlodipine maleate during organogenesis at doses approximately 10 and 20-times the maximum recommended human dose (MRHD), respectively. However for rats, litter size was significantly decreased (by about 50%) and the number of intrauterine deaths was significantly increased (about 5-fold). Amlodipine has been shown to prolong both the gestation period and the duration of labor in rats at this dose [see Data].

The estimated background risk of major birth defects and miscarriage for the indicated population is unknown. All pregnancies have a background risk of birth defect, loss or other adverse outcomes. In the U.S. general population, the estimated background risk of major birth defects and miscarriage in clinically recognized pregnancies is 2%-4% and 15%-20%, respectively.

Clinical Considerations

Disease-associated maternal and/or embryo/fetal risk

Hypertension in pregnancy increases the maternal risk for pre-eclampsia, gestational diabetes, premature delivery, and delivery complications (e.g., need for cesarean section and post-partum hemorrhage). Hypertension increases the fetal risk for intrauterine growth restriction and intrauterine death. Pregnant women with hypertension should be carefully monitored and managed accordingly.

Data

Animal Data

No evidence of teratogenicity or other embryo/fetal toxicity was found when pregnant rats and rabbits were treated orally with amlodipine maleate at doses up to 10 mg amlodipine/kg/day (approximately 10 and 20 times the MRHD based on body surface area, respectively) during their respective periods of major organogenesis. However for rats, litter size was significantly decreased (by about 50%) and the number of intrauterine deaths was significantly increased (about 5-fold) in rats receiving amlodipine maleate at a dose equivalent to 10 mg amlodipine/kg/day for 14 days before mating and throughout mating and gestation. Amlodipine maleate has been shown to prolong both the gestation period and the duration of labor in rats at this dose.

8.2 Lactation

Risk Summary

Limited available data from a published clinical lactation study reports that amlodipine is present in human milk at an estimated median relative infant dose of 4.2%. No adverse effects of amlodipine on the breastfed infant have been observed. There is no available information on the effects of amlodipine on milk production.

8.4 Pediatric Use

Amlodipine (2.5 to 5 mg daily) is effective in lowering blood pressure in patients 6 to 17 years [see Clinical Studies (14.1)] . Effect of amlodipine on blood pressure in patients less than 6 years of age is not known.

8.5 Geriatric Use

Clinical studies of amlodipine did not include sufficient numbers of subjects aged 65 and over to determine whether they respond differently from younger subjects. Other reported clinical experience has not identified differences in responses between the elderly and younger patients. In general, dose selection for an elderly patient should be cautious, usually starting at the low end of the dosing range, reflecting the greater frequency of decreased hepatic, renal, or cardiac function, and of concomitant disease or other drug therapy. Elderly patients have decreased clearance of amlodipine with a resulting increase of AUC of approximately 40–60%, and a lower initial dose may be required [see Dosage and Administration (2.1)] .

8.6 Hepatic Impairment

A lower initial dose may be required for patients with hepatic insufficiency [see Dosage and Administration (2.1) and Clinical Pharmacology (12.3)] .

10 OVERDOSAGE

Overdosage might be expected to cause excessive peripheral vasodilation with marked hypotension and possibly a reflex tachycardia. In humans, experience with intentional overdosage of amlodipine is limited.

Single oral doses of amlodipine maleate equivalent to 40 mg amlodipine/kg and 100 mg amlodipine/kg in mice and rats, respectively, caused deaths. Single oral amlodipine maleate doses equivalent to 4 or more mg amlodipine/kg or higher in dogs (11 or more times the maximum recommended human dose on a mg/m^2basis) caused a marked peripheral vasodilation and hypotension.

If massive overdose should occur, initiate active cardiac and respiratory monitoring. Frequent blood pressure measurements are essential. Should hypotension occur, provide cardiovascular support including elevation of the extremities and the judicious administration of fluids. If hypotension remains unresponsive to these conservative measures, consider administration of vasopressors (such as phenylephrine) with attention to circulating volume and urine output. As amlodipine is highly protein bound, hemodialysis is not likely to be of benefit.

11 DESCRIPTION

KATERZIA oral suspension contains 1.30 mg/mL amlodipine benzoate, equivalent to 1 mg/mL amlodipine, a long-acting calcium channel blocker.

Amlodipine benzoate is chemically described as 3-Ethyl-5-methyl (±)-2-[(2-aminoethoxy) methyl]-4-(2-chlorophenyl)-1,4-dihydro-6-methyl-3,5-pyridinedicarboxylate, benzene-carboxylate. Its empirical formula is C20H25ClN2O5•C7H6O2, and its structural formula is:

Amlodipine benzoate is a white crystalline powder with a molecular weight of 530.

KATERZIA is for oral administration. Inactive ingredients include citric acid, colloidal silicon dioxide, hypromellose, maltodextrin, polysorbate 80, simethicone, sodium benzoate, sodium besylate, sodium citrate, sucralose, and water. It is a white to off-white oral suspension.

12 CLINICAL PHARMACOLOGY

12.1 Mechanism of Action

Amlodipine is a dihydropyridine calcium antagonist (calcium ion antagonist or slow-channel blocker) that inhibits the transmembrane influx of calcium ions into vascular smooth muscle and cardiac muscle. Experimental data suggest that amlodipine binds to both dihydropyridine and nondihydropyridine binding sites. The contractile processes of cardiac muscle and vascular smooth muscle are dependent upon the movement of extracellular calcium ions into these cells through specific ion channels. Amlodipine inhibits calcium ion influx across cell membranes selectively, with a greater effect on vascular smooth muscle cells than on cardiac muscle cells. Negative inotropic effects can be detected in vitrobut such effects have not been seen in intact animals at therapeutic doses. Serum calcium concentration is not affected by amlodipine. Within the physiologic pH range, amlodipine is an ionized compound (pKa=8.6), and its kinetic interaction with the calcium channel receptor is characterized by a gradual rate of association and dissociation with the receptor binding site, resulting in a gradual onset of effect.

Amlodipine is a peripheral arterial vasodilator that acts directly on vascular smooth muscle to cause a reduction in peripheral vascular resistance and reduction in blood pressure.

The precise mechanisms by which amlodipine relieves angina have not been fully delineated, but are thought to include the following:

Exertional Angina: In patients with exertional angina, amlodipine reduces the total peripheral resistance (afterload) against which the heart works and reduces the rate pressure product, and thus myocardial oxygen demand, at any given level of exercise.

Vasospastic Angina: Amlodipine has been demonstrated to block constriction and restore blood flow in coronary arteries and arterioles in response to calcium, potassium epinephrine, serotonin, and thromboxane A2 analog in experimental animal models and in human coronary vessels in vitro. This inhibition of coronary spasm is responsible for the effectiveness of amlodipine in vasospastic (Prinzmetal’s or variant) angina.

12.2 Pharmacodynamics

Hemodynamics: Following administration of therapeutic doses to patients with hypertension, amlodipine produces vasodilation resulting in a reduction of supine and standing blood pressures. These decreases in blood pressure are not accompanied by a significant change in heart rate or plasma catecholamine levels with chronic dosing. Although the acute intravenous administration of amlodipine decreases arterial blood pressure and increases heart rate in hemodynamic studies of patients with chronic stable angina, chronic oral administration of amlodipine in clinical trials did not lead to clinically significant changes in heart rate or blood pressures in normotensive patients with angina.

With chronic once daily oral administration, antihypertensive effectiveness is maintained for at least 24 hours. Plasma concentrations correlate with effect in both young and elderly patients. The magnitude of reduction in blood pressure with amlodipine is also correlated with the height of pretreatment elevation; thus, individuals with moderate hypertension (diastolic pressure 105‑114 mmHg) had about a 50% greater response than patients with mild hypertension (diastolic pressure 90–104 mmHg). Normotensive subjects experienced no clinically significant change in blood pressures (+1/–2 mmHg).

In hypertensive patients with normal renal function, therapeutic doses of amlodipine resulted in a decrease in renal vascular resistance and an increase in glomerular filtration rate and effective renal plasma flow without change in filtration fraction or proteinuria.

As with other calcium channel blockers, hemodynamic measurements of cardiac function at rest and during exercise (or pacing) in patients with normal ventricular function treated with amlodipine have generally demonstrated a small increase in cardiac index without significant influence on dP/dt or on left ventricular end diastolic pressure or volume. In hemodynamic studies, amlodipine has not been associated with a negative inotropic effect when administered in the therapeutic dose range to intact animals and man, even when co-administered with beta-blockers to man. Similar findings, however, have been observed in normal or well-compensated patients with heart failure with agents possessing significant negative inotropic effects.

Electrophysiologic Effects: Amlodipine does not change sinoatrial nodal function or atrioventricular conduction in intact animals or man. In patients with chronic stable angina, intravenous administration of 10 mg did not significantly alter A-H and H-V conduction and sinus node recovery time after pacing. Similar results were obtained in patients receiving amlodipine and concomitant beta-blockers. In clinical studies in which amlodipine was administered in combination with beta-blockers to patients with either hypertension or angina, no adverse effects on electrocardiographic parameters were observed. In clinical trials with angina patients alone, amlodipine therapy did not alter electrocardiographic intervals or produce higher degrees of AV blocks.

12.3 Pharmacokinetics

The exposure (Cmaxand AUC) of KATERZIA oral suspension is similar to that of Norvasc®tablet.

Absorption

After oral administration of therapeutic doses of amlodipine, absorption produces peak plasma concentrations between 6 and 12 hours. Absolute bioavailability has been estimated to be between 64 and 90%.

Effect of Food

Compared to fasted state administration, standard high-fat, high-calorie breakfast did not have a significant effect on the absorption of KATERZIA.

Distribution

Ex vivostudies have shown that approximately 93% of the circulating drug is bound to plasma proteins in hypertensive patients.

Metabolism

Amlodipine is extensively (about 90%) converted to inactive metabolites via hepatic metabolism with 10% of the parent compound and 60% of the metabolites excreted in the urine.

Excretion

Elimination from the plasma is biphasic with a terminal elimination half-life of about 30–50 hours. Steady-state plasma levels of amlodipine are reached after 7 to 8 days of consecutive daily dosing.

Specific Populations

Pediatric Patients

Sixty-two hypertensive patients aged 6 to 17 years received doses of amlodipine between 1.25 mg and 20 mg. Weight-adjusted clearance and volume of distribution were similar to values in adults.

Renal Impairment

The pharmacokinetics of amlodipine are not significantly influenced by renal impairment. Patients with renal failure may therefore receive the usual initial dose.

Hepatic Impairment

Elderly patients and patients with hepatic insufficiency have decreased clearance of amlodipine with a resulting increase in AUC of approximately 40–60%, and a lower initial dose may be required. A similar increase in AUC was observed in patients with moderate to severe heart failure.

Drug Interactions

In vitrodata indicate that amlodipine has no effect on the human plasma protein binding of digoxin, phenytoin, warfarin, and indomethacin.

Impact of Other Drugs on Amlodipine

Co-administered cimetidine, magnesium-and aluminum hydroxide antacids, sildenafil, and grapefruit juice have no impact on the exposure to amlodipine.

CYP3A inhibitors: Co-administration of a 180 mg daily dose of diltiazem with 5 mg amlodipine in elderly hypertensive patients resulted in a 60% increase in amlodipine systemic exposure. Erythromycin co-administration in healthy volunteers did not significantly change amlodipine systemic exposure. However, strong inhibitors of CYP3A (e.g., itraconazole, clarithromycin) may increase the plasma concentrations of amlodipine to a greater extent [see Drug Interactions (7.1)] .

Impact of Amlodipine on Other Drugs

Amlodipine is a weak inhibitor of CYP3A and may increase exposure to CYP3A substrates.

Co-administered amlodipine does not affect the exposure to atorvastatin, digoxin, ethanol, and the warfarin prothrombin response time.

Simvastatin: Co-administration of multiple doses of 10 mg of amlodipine with 80 mg simvastatin resulted in a 77% increase in exposure to simvastatin compared to simvastatin alone [see Drug Interactions (7.2)] .

Cyclosporine: A prospective study in renal transplant patients (N=11) showed on an average of 40% increase in trough cyclosporine levels when concomitantly treated with amlodipine [see Drug Interactions (7.2)] .

Tacrolimus: A prospective study in healthy Chinese volunteers (N=9) with CYP3A5 expressers showed a 2.5- to 4-fold increase in tacrolimus exposure when concomitantly administered with amlodipine compared to tacrolimus alone. This finding was not observed in CYP3A5 non‑expressers (N=6). However, a 3-fold increase in plasma exposure to tacrolimus in a renal transplant patient (CYP3A5 non-expresser) upon initiation of amlodipine for the treatment of post-transplant hypertension resulting in reduction of tacrolimus dose has been reported. Irrespective of the CYP3A5 genotype status, the possibility of an interaction cannot be excluded with these drugs [see Drug Interactions (7.2)] .

13 NONCLINICAL TOXICOLOGY

13.1 Carcinogenesis, Mutagenesis, Impairment of Fertility

Rats and mice treated with amlodipine maleate in the diet for up to two years, at concentrations calculated to provide daily dosage levels of 0.5, 1.25, and 2.5 amlodipine mg/kg/day, showed no evidence of a carcinogenic effect of the drug. For the mouse, the highest dose was, on a mg/m^2basis, similar to the maximum recommended human dose of 10 mg amlodipine/day.^1For the rat, the highest dose was, on a mg/m^2basis, about twice the maximum recommended human dose.^1

Mutagenicity studies conducted with amlodipine maleate revealed no drug related effects at either the gene or chromosome level.

There was no effect on the fertility of rats treated orally with amlodipine maleate (males for 64 days and females for 14 days prior to mating) at doses up to 10 mg amlodipine/kg/day (8 times the maximum recommended human dose^1of 10 mg/day on a mg/m^2basis).

^1Based on patient weight of 50 kg.

14 CLINICAL STUDIES

14.1 Effects in Hypertension

Adult Patients

The antihypertensive efficacy of amlodipine has been demonstrated in a total of 15 double-blind, placebo-controlled, randomized studies involving 800 patients on amlodipine and 538 on placebo. Once daily administration produced statistically significant placebo-corrected reductions in supine and standing blood pressures at 24 hours postdose, averaging about 12/6 mmHg in the standing position and 13/7 mmHg in the supine position in patients with mild to moderate hypertension. Maintenance of the blood pressure effect over the 24-hour dosing interval was observed, with little difference in peak and trough effect. Tolerance was not demonstrated in patients studied for up to 1 year. The 3 parallel, fixed dose, dose response studies showed that the reduction in supine and standing blood pressures was dose-related within the recommended dosing range. Effects on diastolic pressure were similar in young and older patients. The effect on systolic pressure was greater in older patients, perhaps because of greater baseline systolic pressure. Effects were similar in black patients and in white patients.

Pediatric Patients

Two hundred sixty-eight hypertensive patients aged 6 to 17 years were randomized first to amlodipine 2.5 or 5 mg once daily for 4 weeks and then randomized again to the same dose or to placebo for another 4 weeks. Patients receiving 2.5 mg or 5 mg at the end of 8 weeks had significantly lower systolic blood pressure than those secondarily randomized to placebo. The magnitude of the treatment effect is difficult to interpret, but it is probably less than 5 mmHg systolic on the 5 mg dose and 3.3 mmHg systolic on the 2.5 mg dose. Adverse events were similar to those seen in adults.

14.2 Effects in Chronic Stable Angina

The effectiveness of 5–10 mg/day of amlodipine in exercise-induced angina has been evaluated in 8 placebo-controlled, double-blind clinical trials of up to 6 weeks duration involving 1038 patients (684 amlodipine, 354 placebo) with chronic stable angina. In 5 of the 8 studies, significant increases in exercise time (bicycle or treadmill) were seen with the 10 mg dose. Increases in symptom-limited exercise time averaged 12.8% (63 sec) for amlodipine 10 mg, and averaged 7.9% (38 sec) for amlodipine 5 mg. Amlodipine 10 mg also increased time to 1 mm ST segment deviation in several studies and decreased angina attack rate. The sustained efficacy of amlodipine in angina patients has been demonstrated over long-term dosing. In patients with angina, there were no clinically significant reductions in blood pressures (4/1 mmHg) or changes in heart rate (+0.3 bpm).

14.3 Effects in Vasospastic Angina

In a double-blind, placebo-controlled clinical trial of 4 weeks duration in 50 patients, amlodipine therapy decreased attacks by approximately 4/week compared with a placebo decrease of approximately 1/week (p<0.01). Two of 23 amlodipine and 7 of 27 placebo patients discontinued from the study due to lack of clinical improvement.

14.4 Effects in Documented Coronary Artery Disease

In PREVENT, 825 patients with angiographically documented coronary artery disease were randomized to amlodipine (5–10 mg once daily) or placebo and followed for 3 years. Although the study did not show significance on the primary objective of change in coronary luminal diameter as assessed by quantitative coronary angiography, the data suggested a favorable outcome with respect to fewer hospitalizations for angina and revascularization procedures in patients with CAD.

CAMELOT enrolled 1318 patients with CAD recently documented by angiography, without left main coronary disease and without heart failure or an ejection fraction <40%. Patients (76% males, 89% Caucasian, 93% enrolled at US sites, 89% with a history of angina, 52% without PCI, 4% with PCI and no stent, and 44% with a stent) were randomized to double-blind treatment with either amlodipine (5–10 mg once daily) or placebo in addition to standard care that included aspirin (89%), statins (83%), beta-blockers (74%), nitroglycerin (50%), anti‑coagulants (40%), and diuretics (32%), but excluded other calcium channel blockers. The mean duration of follow-up was 19 months. The primary endpoint was the time to first occurrence of one of the following events: hospitalization for angina pectoris, coronary revascularization, myocardial infarction, cardiovascular death, resuscitated cardiac arrest, hospitalization for heart failure, stroke/TIA, or peripheral vascular disease. A total of 110 (16.6%) and 151 (23.1%) first events occurred in the amlodipine and placebo groups, respectively, for a hazard ratio of 0.691 (95% CI: 0.540–0.884, p = 0.003). The primary endpoint is summarized in Figure 1below. The outcome of this study was largely derived from the prevention of hospitalizations for angina and the prevention of revascularization procedures (see Table 1). Effects in various subgroups are shown in Figure 2.

In an angiographic substudy (n=274) conducted within CAMELOT, there was no significant difference between amlodipine and placebo on the change of atheroma volume in the coronary artery as assessed by intravascular ultrasound.

Table 4below summarizes the significant composite endpoint and clinical outcomes from the composites of the primary endpoint. The other components of the primary endpoint including cardiovascular death, resuscitated cardiac arrest, myocardial infarction, hospitalization for heart failure, stroke/TIA, or peripheral vascular disease did not demonstrate a significant difference between amlodipine and placebo.

Table 4: Incidence of Significant Clinical Outcomes
Clinical Outcomes N (%) | Amlodipine (N=663) | Placebo (N=655) | Risk Reduction (p-value)
Composite CV Endpoint | 110 (16.6) | 151 (23.1) | 31% (0.003)
Hospitalization for Angina [Total patients with these events] | 51 (7.7) | 84 (12.8) | 42% (0.002)
Coronary Revascularization | 78 (11.8) | 103 (15.7) | 27% (0.033)

14.5 Studies in Patients with Heart Failure

Amlodipine has been compared to placebo in four 8–12 week studies of patients with NYHA Class II/III heart failure, involving a total of 697 patients. In these studies, there was no evidence of worsened heart failure based on measures of exercise tolerance, NYHA classification, symptoms, or left ventricular ejection fraction. In a long-term (follow-up at least 6 months, mean 13.8 months) placebo-controlled mortality/morbidity study of amlodipine 5–10 mg in 1153 patients with NYHA Classes III (n=931) or IV (n=222) heart failure on stable doses of diuretics, digoxin, and ACE inhibitors, amlodipine had no effect on the primary endpoint of the study which was the combined endpoint of all-cause mortality and cardiac morbidity (as defined by life-threatening arrhythmia, acute myocardial infarction, or hospitalization for worsened heart failure), or on NYHA classification, or symptoms of heart failure. Total combined all-cause mortality and cardiac morbidity events were 222/571 (39%) for patients on amlodipine and 246/583 (42%) for patients on placebo; the cardiac morbid events represented about 25% of the endpoints in the study.

In another study, (PRAISE-2) randomized patients with NYHA Class III (80%) or IV (20%) heart failure without clinical symptoms or objective evidence of underlying ischemic disease, on stable doses of ACE inhibitors (99%), digitalis (99%), and diuretics (99%), to placebo (n=827) or amlodipine (n=827) and followed them for a mean of 33 months. There was no statistically significant difference between amlodipine and placebo in the primary endpoint of all-cause mortality (95% confidence limits from 8% reduction to 29% increase on amlodipine). With amlodipine there were more reports of pulmonary edema.

16 HOW SUPPLIED/STORAGE AND HANDLING

KATERZIA (amlodipine) is a white to off-white, aqueous oral suspension that contains 1 mg of amlodipine per milliliter (equivalent to 1.30 mg of amlodipine benzoate). It is supplied as 150 mL in a 185 mL high-density polyethylene (HDPE) bottle with a child-resistant cap and tamper-evident seal. SHAKE BEFORE USING.

NDC 52652-5001-1

Storage

KATERZIA (amlodipine) oral suspension, 1 mg/mL, should be stored refrigerated (2°C to 8°C/36°F to 46°F). Avoid freezing and excessive heat. Protect from light.

Manufactured for:
Azurity Pharmaceuticals, Inc.
Woburn, MA 01801 USA

Patent: https://azurity.com/patents

This product’s label may have been updated. For current Full Prescribing Information, please visit katerzia.com

PI500101-04 Rev. 4/2023

PRINCIPAL DISPLAY PANEL - Bottle Label

NDC 52652-5001-1

Katerzia®
(amlodipine)
Oral Suspension
1 mg/mL

150 mL Rx Only

azurity™
pharmaceuticals

70040042

KEEP THIS AND ALL
MEDICATIONS
OUT OF THE REACH
OF CHILDREN.

Manufactured for:
Azurity Pharmaceuticals, Inc.
Wilmington, MA 01887 USA

Each 1 mL contains 1 mg amlodipine
(equivalent to 1.30 mg amlodipine
benzoate).

Usual Dose:
See prescribing information.

Shake before using.

Must store refrigerated:
2° - 8°C (36° - 46°F).

Protect from light.
Avoid excessive heat and freezing.